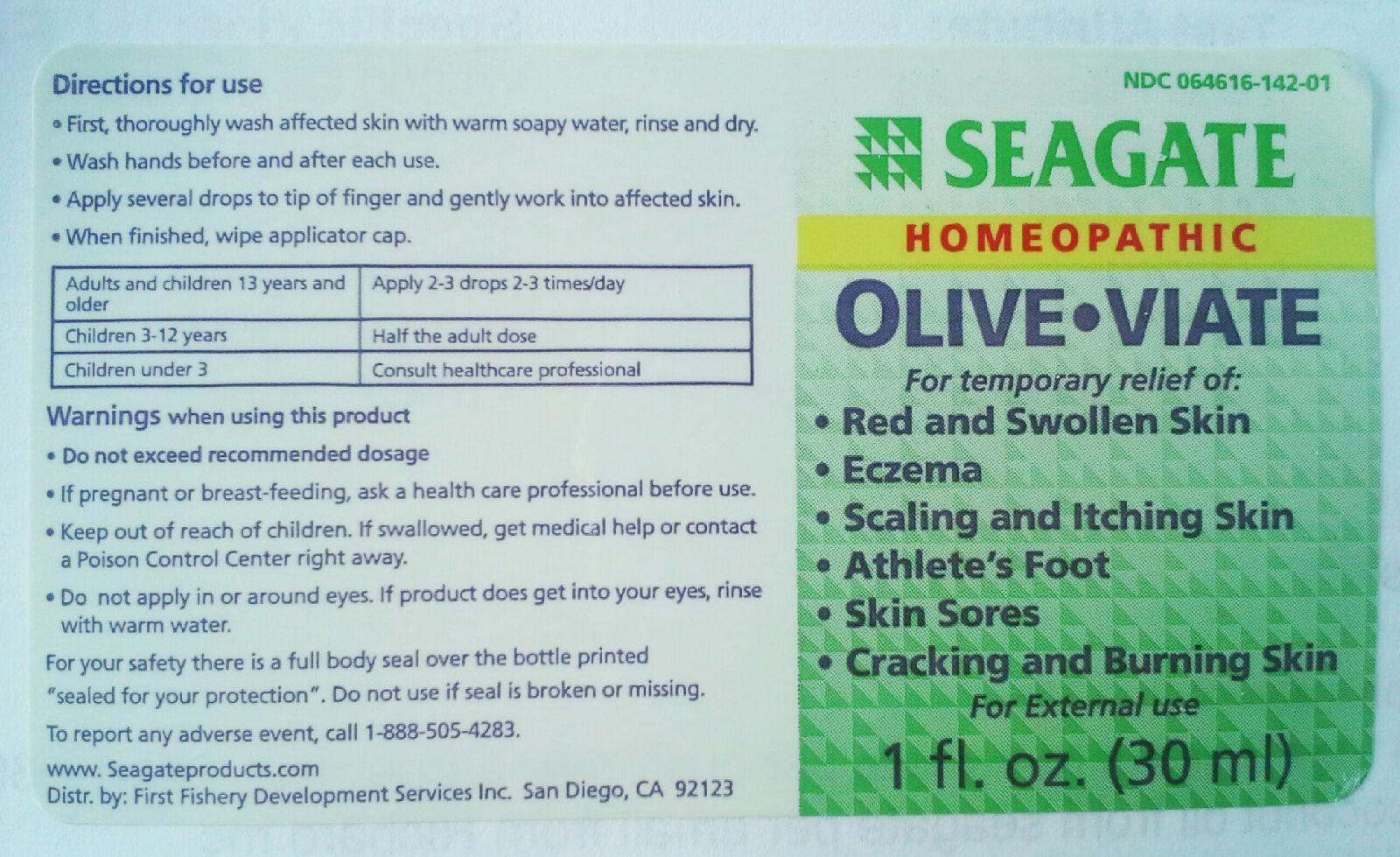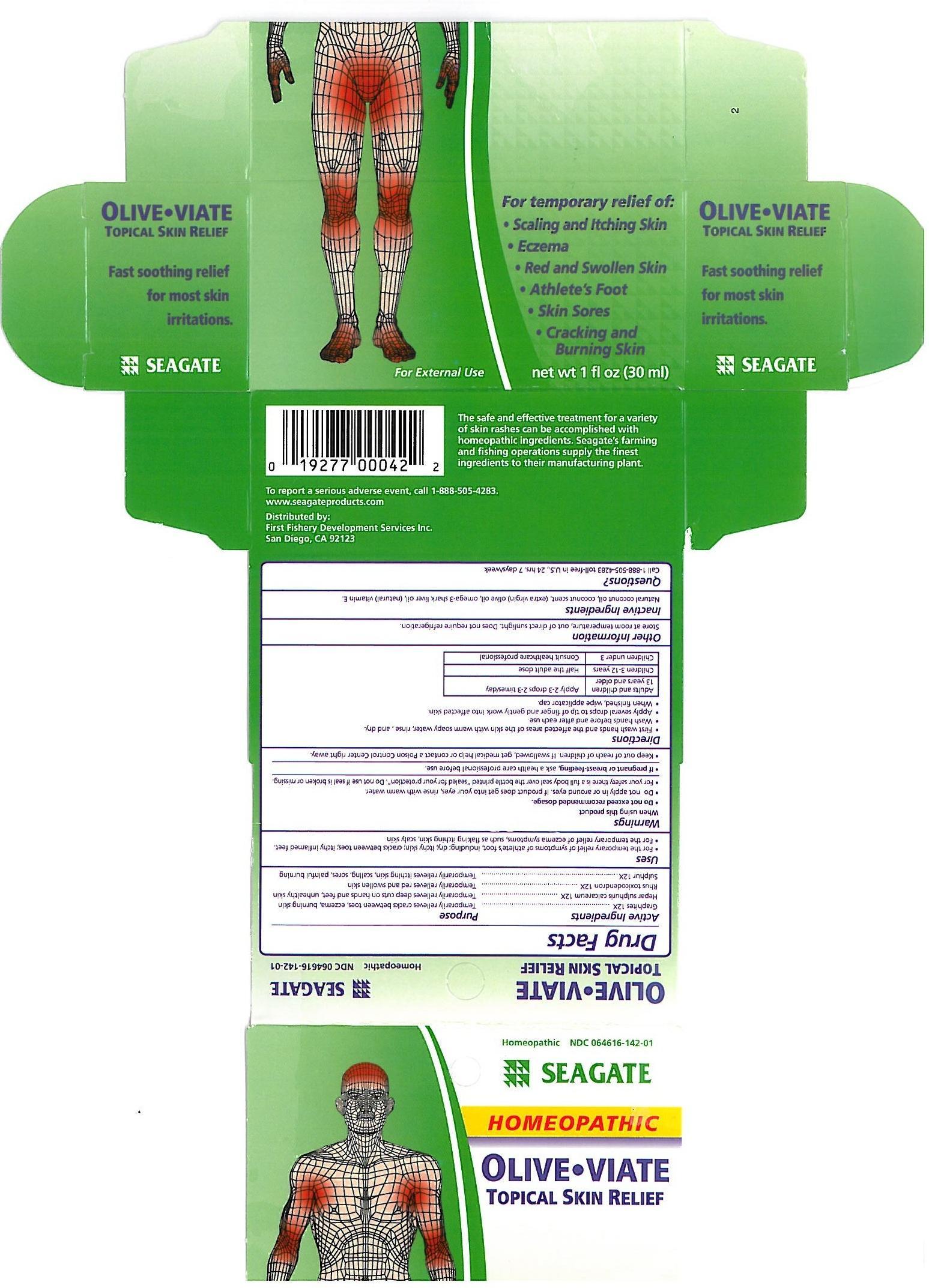 DRUG LABEL: Olive-Viate
NDC: 64616-042 | Form: LIQUID
Manufacturer: Vitality Works, Inc.
Category: homeopathic | Type: HUMAN OTC DRUG LABEL
Date: 20251217

ACTIVE INGREDIENTS: GRAPHITE 12 [hp_X]/1 mL; CALCIUM SULFIDE 12 [hp_X]/1 mL; TOXICODENDRON PUBESCENS LEAF 12 [hp_X]/1 mL; SULFUR 12 [hp_X]/1 mL
INACTIVE INGREDIENTS: COCONUT OIL; OLIVE OIL; SHARK LIVER OIL; ALPHA-TOCOPHEROL ACETATE

Olive-Viate

Olive-Viate

Graphites 12X

Hepar sulphuris calcareum 12X

Rhus toxicodendron 12X

Sulphur 12X

Olive-Viate

Natural coconut oil, coconut scent, extra virgin olive Oil, Omega-3 fish liver Oil, Natural Vitamin E

Olive-Viate

Do not exceed recommended dosage. Do not apply in or around eyes. If product does get into your eyes, rinse with warm water. For your safety there is a full body seal over the bottle printed "sealed for your protection". Do not use if seal is broken or missing.

Olive-Viate

Keep out of reach of children. If swallowed, get medical help or contact a Poison Control Center right away.

Olive-Viate

For the temporary relief of symptoms of athlete's foot, including dry, itchy skin, cracks between toes; itchy inflamed feet.

For the temporary relief of eczema symptoms, such as flaking itching skin, scaly skin.

Olive-Viate

First wash hands and the affected areas of the skin with warm soapy water, rinse, and dry.

Wash hands before and after each use.

Apply several drops to tip of finger and gently work into affected skin.

When finished, wipe applicator cap.

Adults and children 13 years and older: Apply 1-3 drops 2-3 times a day.

Children 3-12 years: Half the adult dose.

Childern under 3: Consult healthcare professional.

Olive-Viate

Graphites - temporarily relieves cracks between toes, eczema burning skin.

Hepar sulphuris calcareum - temporily relieves deep cuts on hands and feet, unhealthy skin.

Rhus toxicodendron - Temporarily relieves red and swollen skin.

Sulphur - temporarily relieves itchy skin, scaling sores, painful burning.,